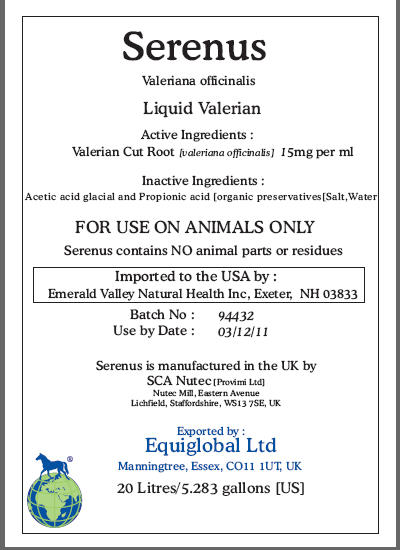 DRUG LABEL: Serenus
NDC: 52338-397 | Form: EXTRACT
Manufacturer: SCA NuTec
Category: animal | Type: PRESCRIPTION ANIMAL DRUG LABEL
Date: 20100419

ACTIVE INGREDIENTS: VALERIAN 15 mg/1 mL

Serenus

Valeriana officinalis
Liquid Valerian

Active Ingredients:

Valerian Cut Root [valeriana officinalis] 15mg per ml

Inactive Ingredients:

Acetic acid glacial and Propionic acid [organic preservatives[Salt,Water

WARNINGS

FOR USE ON ANIMALS ONLY

Serenus contains NO animal parts or residues

Serenus contains NO animal parts or residues
Imported to the USA by :
Emerald Valley Natural Health Inc, Exeter, NH 03833
Batch No: 94432
Use by Date: 03/12/11
Serenus is manufactured in the UK by
SCA Nutec [Provimi Ltd]
Nutec Mill, Eastern Avenue
Lichfield, Staffordshire, WS13 7SE, UK
Exported by :
Equiglobal Ltd
Manningtree, Essex, CO11 1UT, UK
20 Litres/5.283 gallons [US]